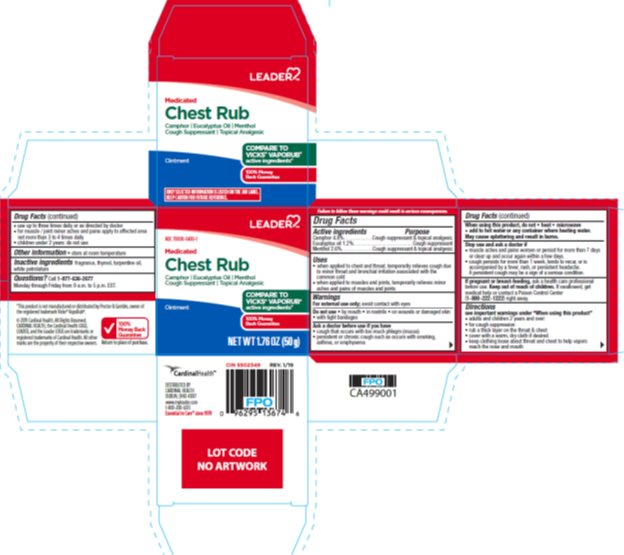 DRUG LABEL: Medicated Chest Rub
NDC: 70000-0480 | Form: OINTMENT
Manufacturer: Cardinal Health, 110 dba LEADER
Category: otc | Type: HUMAN OTC DRUG LABEL
Date: 20251212

ACTIVE INGREDIENTS: CAMPHOR (SYNTHETIC) 48 mg/1 g; EUCALYPTUS OIL 12 mg/1 g; MENTHOL, UNSPECIFIED FORM 26 mg/1 g
INACTIVE INGREDIENTS: THYMOL; TURPENTINE; PETROLATUM

Drug Facts - Cardinal Health Medicated Chest Rub

Active ingredients

Camphor 4.8%

Eucalyptus oil 1.2%

Menthol 2.6%

Purpose

Camphor - Cough suppressant & topical analgesic

Eucalyptus oil - Cough suppressant

Menthol - Cough suppressant & topical analgesic

Uses

- when applied to chest and throat, temporarily relieves cough due to minor throat and bronchial irritation associated with the common cold
- when applied to muscles and joints, temporarily relieves minor aches and pains of muscles and joints

Warnings

For external use only; avoid contact with eyes

Do not use

- by mouth
- in nostrils
- on wounds or damaged skin
- with tight bandages

Ask a doctor before use if you have

- cough that occurs with too much phlegm (mucus)
- persistent or chronic cough such as occurs with smoking, asthma, or emphysema

When using this product, do not

heat, microwave, or add to hot water or any container where heating water. May cause splattering and result in burns.

Stop use and ask a doctor if

- muscle aches and pains worsen, persist for more than 7 days, or clear up and occur again within a few days
- cough persists for more than 1 week, tends to recur, or is accompanied by fever, rash, or persistent headache. A persistent cough could be a sign of a serious condition.

If pregnant or breast-feeding,

ask a health professional before use.

Keep out of reach of children.

- If swallowed, get medical help or contact a Poison Control Center (1-800-222-1222) right away.

Directions

- see important warning under "When using this product"
- adults and children 2 years and over:
- for cough suppression
- rub a thick layer on the throat & chest
- cover with a warm, dry cloth if desired
- keep clothing loose about throat and chest to help vapors reach the nose and mouth
- use up to three times daily, or as directed by a doctor
- for muscle / joint minor aches and pains, apply to affected area not more than 3 to 4 times daily
- children under 2 years: do not use

Inactive ingredients

fragrance, thymol, turpentine oil, white petrolatum

Questions?

Call: 1-877-636-2677 Monday through Friday from 9 a.m. to 5 p.m. EST .